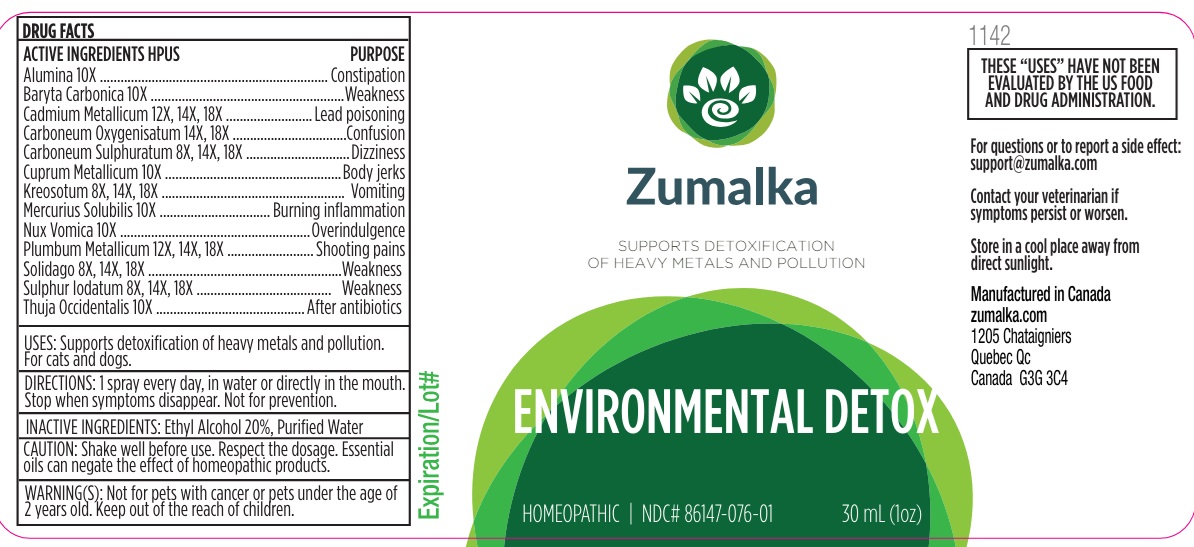 DRUG LABEL: ENVIRONMENTAL DETOX
NDC: 86147-076 | Form: LIQUID
Manufacturer: Groupe Cyrenne Inc.
Category: homeopathic | Type: OTC ANIMAL DRUG LABEL
Date: 20251120

ACTIVE INGREDIENTS: ALUMINUM OXIDE 10 [hp_X]/30 mL; BARIUM CARBONATE 10 [hp_X]/30 mL; CADMIUM 12 [hp_X]/30 mL; CARBON MONOXIDE 14 [hp_X]/30 mL; CARBON DISULFIDE 8 [hp_X]/30 mL; COPPER 10 [hp_X]/30 mL; WOOD CREOSOTE 8 [hp_X]/30 mL; MERCURIUS SOLUBILIS 10 [hp_X]/30 mL; STRYCHNOS NUX-VOMICA SEED 10 [hp_X]/30 mL; SOLIDAGO VIRGAUREA FLOWERING TOP 8 [hp_X]/30 mL; THUJA OCCIDENTALIS LEAFY TWIG 10 [hp_X]/30 mL; SULFUR IODIDE 8 [hp_X]/30 mL; LEAD 12 [hp_X]/30 mL
INACTIVE INGREDIENTS: ALCOHOL; WATER

Active ingredients Purpose

Alumina 10x ……………………………….Constipation
Baryta Carbonica 10x …………………….Weakness
Cadmium Metallicum 12x, 14x, 18x …….Lead poisoning
Carboneum Oxygenisatum 14x, 18x ……Confusion
Carboneum Sulphuratum 8x, 14x, 18x ….Dizziness
Cuprum Metallicum 10x …………………..Body jerks
Kreosotum 8x, 14x, 18x …………………..Vomiting
Mercurius Solubilis 10x,............................ Burning inflammation
Nux Vomica 10x ……………………………Overindulgence
Plumbum Metallicum 12x, 14x, 18x ………Shooting pains
Solidago 8x, 14x, 18x ………………………Weakness
Sulphur Iodatum 8x, 14x, 18x ……………..Weight loss
Thuja Occidentalis 10x …………………….After antibiotics

Uses

Supports detoxification of heavy metals and pollution. For cats and dogs

Warnings

Keep out of reach of children. Not for pets with cancer or pets under the age of 2 years old.

Direction

1 spray every day, in water or directly in the mouth. Stop when symptoms disappear.

Inactive ingredients

Ethyl alcohol 20%, purified water

Cautions

Shake well before use. Respect the dosage. Essential oils can negate the effects of homeopathic products. Store in a cool place away from direct sunlight.